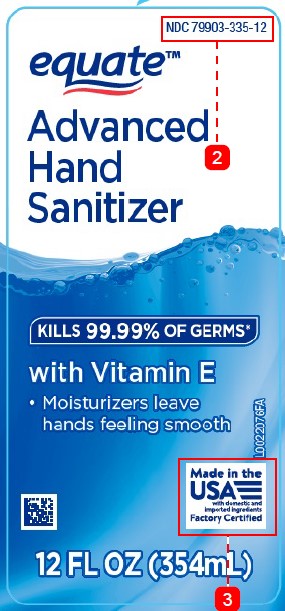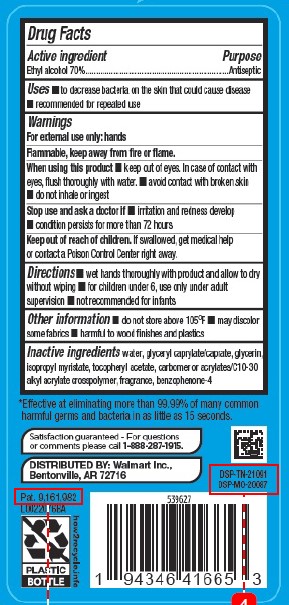 DRUG LABEL: Hand Sanitizer
NDC: 79903-335 | Form: GEL
Manufacturer: Walmart Inc.
Category: otc | Type: HUMAN OTC DRUG LABEL
Date: 20260227

ACTIVE INGREDIENTS: ALCOHOL 70 mL/100 mL
INACTIVE INGREDIENTS: WATER; GLYCERYL CAPRYLATE/CAPRATE; GLYCERIN; ISOPROPYL MYRISTATE; .ALPHA.-TOCOPHEROL ACETATE; CARBOMER HOMOPOLYMER, UNSPECIFIED TYPE; CARBOMER COPOLYMER TYPE B (ALLYL PENTAERYTHRITOL CROSSLINKED); SULISOBENZONE

Equate 370.001-370AB-AE rev 1
Advanced Hand Sanitizer

Active Ingredient

Ethyl alcohol 70%

Purpose

Antiseptic

Uses

- to decrease bacteria on the skin that could cause disease
- recommended for repeated use

Warnings

For external use only: hands

Flammable. Keep away from fire or flame.

When using this product

- keep out of eyes. In case of contact with eyes, flush thoroughly with water.
- avoid contact with broken skin
- do not inhale or ingest

Stop use and ask a doctor if

- irritation and redness develop
- condition persists for more than 72 hours

Keep out of reach of children.

If swallowed, get medical help or contact a Poison Control Center right away.

Directions

- wet hands thoroughly with product and allow to dry without wiping
- for children under 6, use only under adult supervision
- not recommended for infants

Other information

- do not store above 105⁰ F
- may discolor some fabrics
- harmful to wood finishes and plastics

Inactive ingredients

water, glyceryl caprylate/caprate, glycerin, isopropyl myristate, tocopheryl acetate, acrylates/C10-30 alkyl acrylate crosspolymer, fragrance, benzophenone-4

Claims

*Effective at eliminating more than 99.99% of many common harmful germs and bacteria in as little as 15 seconds.

ADVERSE REACTION

Satisfaction guaranteed - For questions or comments please call 1-888-287-1915.

DISTRIBUTED BY: Walmart Inc.,

Bentonville, AR 72716

DSP-TN-21091

DSP-MO-20087

Pat. 9,161,982

PLASTIC BOTTLE

how2recycle.info

PRINCIPAL DISPLAY PANEL

NDC 79903-335-12

equate™

Advanced

Hand

Sanitizer

KILLS 99.99% OF GERMS*

with Vitamin E

- Moisturizers leave hands feeling smooth

Made in the USA with domestic and imported ingredients

Factory Certified

12 FL OZ (354mL)